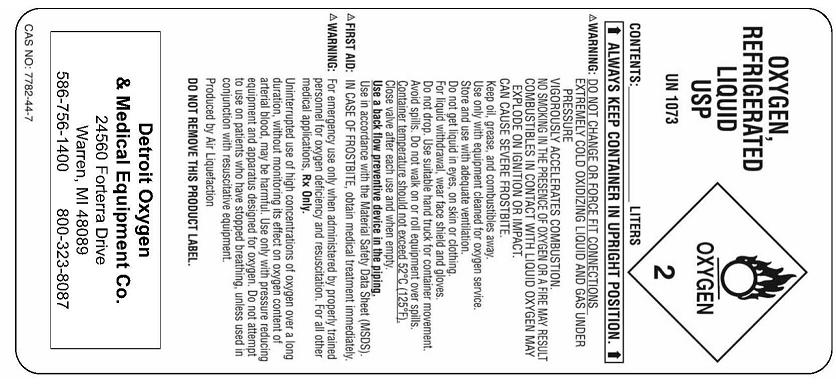 DRUG LABEL: Oxygen
NDC: 59460-0001 | Form: GAS
Manufacturer: Detroit Oxygen & Medical Equipment Co.
Category: prescription | Type: HUMAN PRESCRIPTION DRUG LABEL
Date: 20091218

ACTIVE INGREDIENTS: Oxygen 99 L/100 L

Oxygen